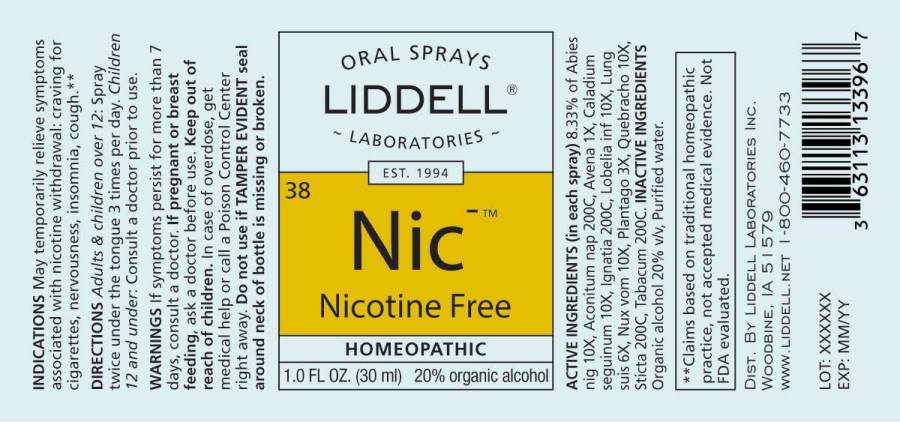 DRUG LABEL: Nicotine Free
NDC: 50845-0267 | Form: SPRAY
Manufacturer: Liddell Laboratories, Inc.
Category: homeopathic | Type: HUMAN OTC DRUG LABEL
Date: 20241104

ACTIVE INGREDIENTS: PICEA MARIANA RESIN 10 [hp_X]/1 mL; ACONITUM NAPELLUS WHOLE 200 [hp_C]/1 mL; AVENA SATIVA FLOWERING TOP 1 [hp_X]/1 mL; DIEFFENBACHIA SEGUINE WHOLE 10 [hp_X]/1 mL; STRYCHNOS IGNATII SEED 200 [hp_C]/1 mL; LOBELIA INFLATA WHOLE 10 [hp_X]/1 mL; SUS SCROFA LUNG 6 [hp_X]/1 mL; STRYCHNOS NUX-VOMICA SEED 10 [hp_X]/1 mL; PLANTAGO MAJOR WHOLE 3 [hp_X]/1 mL; ASPIDOSPERMA QUEBRACHO-BLANCO BARK 10 [hp_X]/1 mL; LOBARIA PULMONARIA 200 [hp_C]/1 mL; TOBACCO LEAF 200 [hp_C]/1 mL
INACTIVE INGREDIENTS: WATER; ALCOHOL

DRUG FACTS:

ACTIVE INGREDIENTS:

(in each spray) 8.33% of Abies Nigra 10X, Aconitum Napellus 200C, Avena Sativa 1X, Caladium Seguinum 10X, Ignatia Amara 200C, Lobelia Inflata 10X, Lung Suis 6X, Nux Vomica 10X, Plantago Major 3X, Quebracho 10X, Sticta Pulmonaria 200C, Tabacum 200C.

INDICATIONS:

May temporarily relieve symptoms associated with nicotine withdrawal: craving for cigarettes, nervousness, insomnia, cough.**

**Claims based on traditional homeopathic practice, not accepted medical evidence. Not FDA evaluated.

WARNINGS:

If symptoms persist for more than 7 days, consult a doctor.

If pregnant or breast-feeding, ask a doctor before use.

Keep out of reach of children. In case of overdose, get medical help or call a Poison Control Center right away.

Do not use if TAMPER EVIDENT seal around neck of bottle is missing or broken.

Keep out of reach of children. In case of overdose, get medical help or call a Poison Control Center right away.

DIRECTIONS:

Adults & children over 12: Spray twice under the tongue 3 times per day.

Children under 12: Consult a doctor prior to use.

INDICATIONS:

May temporarily relieve symptoms associated with nicotine withdrawal: craving for cigarettes, nervousness, insomnia, cough.**

**Claims based on traditional homeopathic practice, not accepted medical evidence. Not FDA evaluated.

INACTIVE INGREDIENTS:

Organic Alcohol 20% v/v, Purified water.

QUESTIONS:

DIST. BY LIDDELL LABORATORIES INC.

WOODBINE, IA 51579

WWW.LIDDELL.NET 1-800-460-7733

PACKAGE DISPLAY LABEL:

ORAL SPRAYS

LIDDELL LABORATORIES

EST. 1994

38 Nic

Nicotine Free

HOMEOPATHIC

1.0 FL OZ (30 ml)